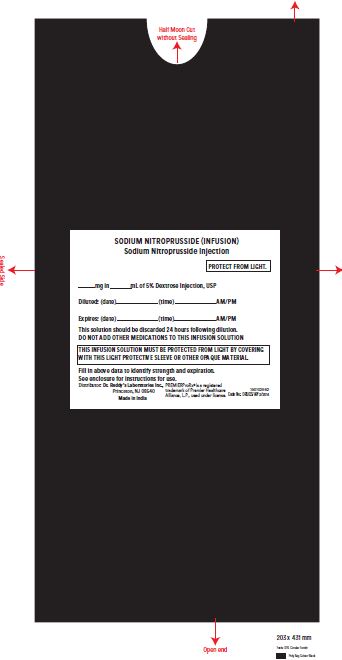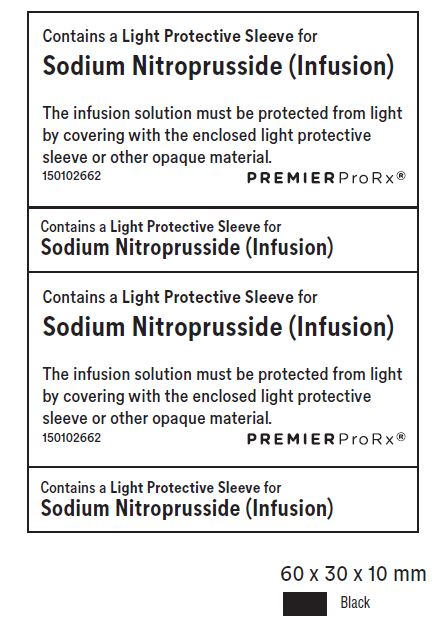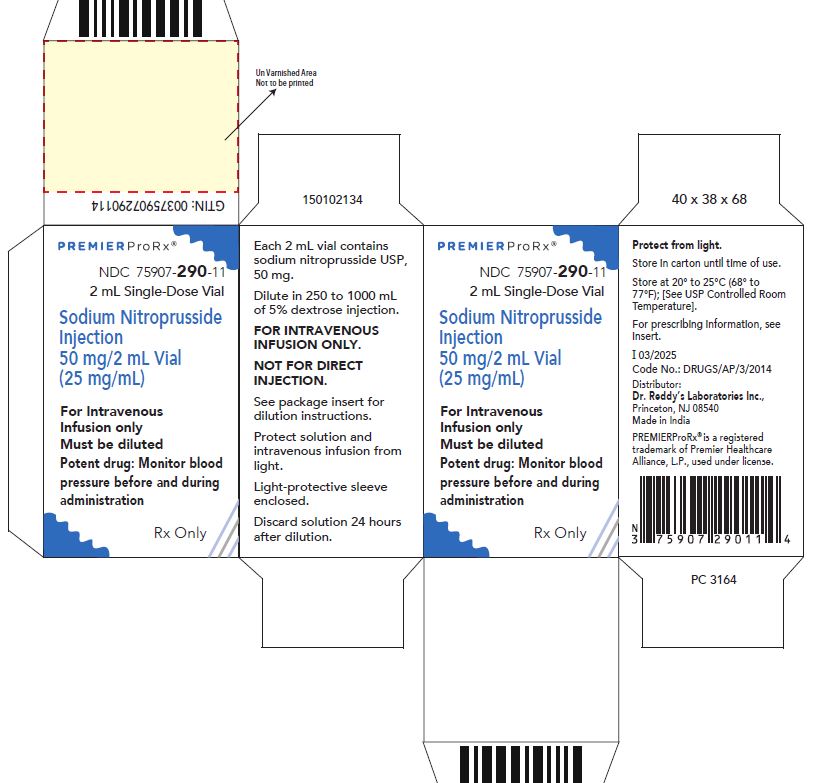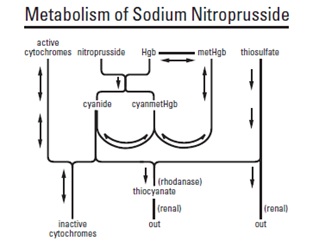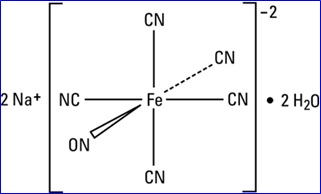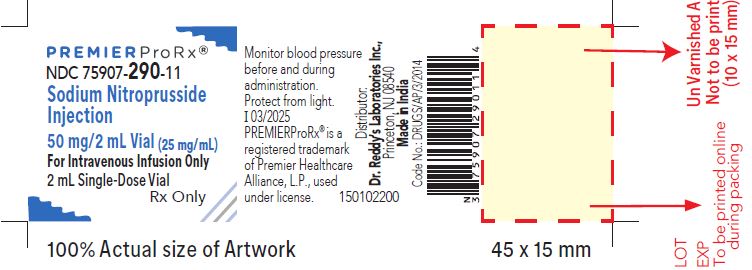 DRUG LABEL: Sodium Nitroprusside
NDC: 75907-290 | Form: INJECTION, SOLUTION
Manufacturer: Dr.Reddy's Laboratories Inc.,
Category: prescription | Type: HUMAN PRESCRIPTION DRUG LABEL
Date: 20251117

ACTIVE INGREDIENTS: Sodium Nitroprusside 50 mg/2 mL
INACTIVE INGREDIENTS: Water

Sodium Nitroprusside Injection

BOXED WARNING

Sodium Nitroprusside Injection is not suitable for direct injection. The solution must be further diluted in sterile 5% dextrose injection before infusion.
Sodium nitroprusside can cause precipitous decreases in blood pressure (see DOSAGE AND ADMINISTRATION). In patients not properly monitored, these decreases can lead to irreversible ischemic injuries or death. Sodium nitroprusside should be used only when available equipment and personnel allow blood pressure to be continuously monitored. Except when used briefly or at low (<2 mcg/kg/min) infusion rates, sodium nitroprusside gives rise to important quantities of cyanide ion, which can reach toxic, potentially lethal levels (see WARNINGS).

The usual dose rate is 0.5 to10 mcg/kg/min, but infusion at the maximum dose rate should never last more than 10 minutes. If blood pressure has not been adequately controlled after 10 minutes of infusion at the maximum rate, administration of sodium nitroprusside should be terminated immediately.

Although acid-base balance and venous oxygen concentration should be monitored and may indicate cyanide toxicity, these laboratory tests provide imperfect guidance.

DESCRIPTION

Sodium nitroprusside is disodium pentacyanonitrosylferrate(2-) dihydrate, a hypotensive agent whose structural formula is

Sodium Nitroprusside

whose molecular formula is Na2[Fe(CN)5NO] • 2H2O, and whose molecular weight is 297.95. Dry sodium nitroprusside is a reddish-brown powder, soluble in water. In an aqueous solution infused intravenously, sodium nitroprusside is a rapid-acting vasodilator, active on both arteries and veins.

Sodium nitroprusside solution is rapidly degraded by trace contaminants, often with resulting color changes. (See DOSAGE AND ADMINISTRATION section.) The solution is also sensitive to certain wavelengths of light, and it must be protected from light in clinical use.

Sodium Nitroprusside Injection is available as:

50 mg Vial – Each 2 mL vial contains the equivalent of 50 mg sodium nitroprusside dihydrate in sterile water for injection.

CLINICAL PHARMACOLOGY

The principal pharmacological action of sodium nitroprusside is relaxation of vascular smooth muscle and consequent dilatation of peripheral arteries and veins. Other smooth muscle (e.g., uterus, duodenum) is not affected. Sodium nitroprusside is more active on veins than on arteries, but this selectivity is much less marked than that of nitroglycerin. Dilatation of the veins promotes peripheral pooling of blood and decreases venous return to the heart, thereby reducing left ventricular end diastolic pressure and pulmonary capillary wedge pressure (preload). Arteriolar relaxation reduces systemic vascular resistance, systolic arterial pressure, and mean arterial pressure (afterload). Dilatation of the coronary arteries also occurs.

In association with the decrease in blood pressure, sodium nitroprusside administered intravenously to hypertensive and normotensive patients produces slight increases in heart rate and a variable effect on cardiac output. In hypertensive patients, moderate doses induce renal vasodilatation roughly proportional to the decrease in systemic blood pressure, so there is no appreciable change in renal blood flow or glomerular filtration rate.

In normotensive subjects, acute reduction of mean arterial pressure to 60 to 75 mm Hg by infusion of sodium nitroprusside caused a significant increase in renin activity. In the same study, ten renovascular-hypertensive patients given sodium nitroprusside had significant increases in renin release from the involved kidney at mean arterial pressures of 90 to 137 mm Hg.

The hypotensive effect of sodium nitroprusside is seen within a minute or two after the start of an adequate infusion, and it dissipates almost as rapidly after an infusion is discontinued. The effect is augmented by ganglionic blocking agents and inhaled anesthetics.

Pharmacokinetics and Metabolism: Infused sodium nitroprusside is rapidly distributed to a volume that is approximately coextensive with the extracellular space. The drug is cleared from this volume by intraerythrocytic reaction with hemoglobin (Hgb), and sodium nitroprusside’s resulting circulatory half-life is about 2 minutes.

The products of the nitroprusside/hemoglobin reaction are cyanmethemoglobin (cyanmetHgb) and cyanide ion (CN^–). Safe use of sodium nitroprusside injection must be guided by knowledge of the further metabolism of these products.

As shown in the diagram below, the essential features of nitroprusside metabolism are

• one molecule of sodium nitroprusside is metabolized by combination with hemoglobin to produce one molecule of cyanmethemoglobin and four CN^– ions;

• methemoglobin, obtained from hemoglobin, can sequester cyanide as cyanmethemoglobin;

• thiosulfate reacts with cyanide to produce thiocyanate;

• thiocyanate is eliminated in the urine;

• cyanide not otherwise removed binds to cytochromes; and

• cyanide is much more toxic than methemoglobin or thiocyanate.

Cyanide ion is normally found in serum; it is derived from dietary substrates and from tobacco smoke. Cyanide binds avidly (but reversibly) to ferric ion (Fe+++), most body stores of which are found in erythrocyte methemoglobin (metHgb) and in mitochondrial cytochromes. When CN^– is infused or generated within the bloodstream, essentially all of it is bound to methemoglobin until intraerythrocytic methemoglobin has been saturated.

When the Fe^+++ of cytochromes is bound to cyanide, the cytochromes are unable to participate in oxidative metabolism. In this situation, cells may be able to provide for their energy needs by utilizing anaerobic pathways, but they thereby generate an increasing body burden of lactic acid. Other cells may be unable to utilize these alternative pathways, and they may die hypoxic deaths. CN^– levels in packed erythrocytes are typically less than 1 μmol/L (less than 25 mcg/L); levels are roughly doubled in heavy smokers.

At healthy steady state, most people have less than 1% of their hemoglobin in the form of methemoglobin.

Nitroprusside metabolism can lead to methemoglobin formation (a) through dissociation of cyanmethemoglobin formed in the original reaction of sodium nitroprusside with Hgb and (b) by direct oxidation of Hgb by the released nitroso group. Relatively large quantities of sodium nitroprusside, however, are required to produce significant methemoglobinemia.

At physiologic methemoglobin levels, the CN^– binding capacity of packed red cells is a little less than 200 μmol/L (5 mg/L). Cytochrome toxicity is seen at levels only slightly higher, and death has been reported at levels from 300 to 3000 μmol/L (8–80 mg/L). Put another way, a patient with a normal red-cell mass (35 mL/kg) and normal methemoglobin levels can buffer about 175 mcg/kg of CN^–, corresponding to a little less than 500 mcg/kg of infused sodium nitroprusside.

Some cyanide is eliminated from the body as expired hydrogen cyanide, but most is enzymatically converted to thiocyanate (SCN^–) by thiosulfate-cyanide sulfur transferase (rhodanase, EC 2.8.1.1), a mitochondrial enzyme. The enzyme is normally present in great excess, so the reaction is rate-limited by the availability of sulfur donors, especially thiosulfate, cystine, and cysteine.

Thiosulfate is a normal constituent of serum, produced from cysteine by way of β-mercaptopyruvate. Physiological levels of thiosulfate are typically about 0.1 mmol/L (11 mg/L), but they are approximately twice this level in pediatric and adult patients who are not eating. Infused thiosulfate is cleared from the body (primarily by the kidneys) with a half-life of about 20 minutes.

When thiosulfate is being supplied only by normal physiologic mechanisms, conversion of CN^– to SCN^– generally proceeds at about 1 mcg/kg/min. This rate of CN^– clearance corresponds to steady-state processing of a sodium nitroprusside infusion of slightly more than 2 mcg/kg/min. CN^– begins to accumulate when sodium nitroprusside infusions exceed this rate.

Thiocyanate (SCN^–) is also a normal physiological constituent of serum, with normal levels typically in the range of 50 to 250 μmol/L (3 to 15 mg/L). Clearance of SCN^– is primarily renal, with a half-life of about 3 days. In renal failure, the half-life can be doubled or tripled.

CLINICAL TRIALS

Baseline-controlled clinical trials have uniformly shown that sodium nitroprusside has a prompt hypotensive effect, at least initially, in all populations. With increasing rates of infusion, sodium nitroprusside has been able to lower blood pressure without an observed limit of effect.

Clinical trials have also shown that the hypotensive effect of sodium nitroprusside is associated with reduced blood loss in a variety of major surgical procedures.

In patients with acute congestive heart failure and increased peripheral vascular resistance, administration of sodium nitroprusside causes reductions in peripheral resistance, increases in cardiac output, and reductions in left ventricular filling pressure.

Many trials have verified the clinical significance of the metabolic pathways described above. In patients receiving unopposed infusions of sodium nitroprusside, cyanide and thiocyanate levels have increased with increasing rates of sodium nitroprusside infusion. Mild to moderate metabolic acidosis has usually accompanied higher cyanide levels, but peak base deficits have lagged behind the peak cyanide levels by an hour or more.

Progressive tachyphylaxis to the hypotensive effects of sodium nitroprusside has been reported in several trials and numerous case reports. This tachyphylaxis has frequently been attributed to concomitant cyanide toxicity, but the only evidence adduced for this assertion has been the observation that in patients treated with sodium nitroprusside and found to be resistant to its hypotensive effects, cyanide levels are often found to be elevated. In the only reported comparisons of cyanide levels in resistant and nonresistant patients, cyanide levels did not correlate with tachyphylaxis. The mechanism of tachyphylaxis to sodium nitroprusside remains unknown.

Pediatric:

The effects of sodium nitroprusside to induce hypotension were evaluated in two trials in pediatric patients less than 17 years of age. In both trials, at least 50% of the patients were pre-pubertal, and about 50% of these pre-pubertal patients were less than 2 years of age, including 4 neonates. The primary efficacy variable was the mean arterial pressure (MAP).

There were 203 pediatric patients in a parallel, dose-ranging study (Study 1). During the 30 minute blinded phase, patients were randomized 1:1:1:1 to receive sodium nitroprusside 0.3, 1, 2, or 3 μg/kg/min. The infusion rate was increased step-wise to the target dose rate (i.e., 1/3 of the full rate for the first 5 minutes, 2/3 of the full rate for the next 5 minutes, and the full dose rate for the last 20 minutes). If the investigator believed that an increase to the next higher dose rate would be unsafe, the infusion remained at the current rate for the remainder of the blinded infusion. Since there was no placebo group, the change from baseline likely overestimates the true magnitude of blood pressure effect. Nevertheless, MAP decreased 11 to 20 mmHg from baseline across the four doses (Table 1).

There were 63 pediatric patients in a long-term infusion trial (Study 2). During an open-label phase (12 to 24 hours), sodium nitroprusside was started at ≤0.3 μg/kg/min and titrated according to the BP response.

Patients were then randomized to placebo or to continuing the same dose of sodium nitroprusside. The average MAP was greater in the control group than in the sodium nitroprusside group for every time point during the blinded withdrawal phase, demonstrating that sodium nitroprusside is effective for at least 12 hours.

In both studies, similar effects on MAP were seen in all age groups.

Table 1: Change from Baseline in MAP (mmHg) After 30 Minutes Double-Blind Infusion (Study 1)

 |  | Treatment
Endpoint | 0.3 µg/kg/min (N = 50) | 1 µg/kg/min (N = 49) | 2 µg/kg/min (N = 53) | 3 µg/kg/min (N = 51)
Baseline | 76 ± 11 | 77 ± 15 | 74 ± 12 | 76 ± 12
30 Min | 65 ± 13 | 60 ± 15 | 54 ± 12 | 60 ± 18
Change from Baseline | -11 ± 16 (-15, -6.5) | -17 ± 13 (-21, -13) | -20 ± 16 (-24, -16) | -17 ± 19 (-22, -11)

Mean ± SD (95% CI)

INDICATIONS AND USAGE

Sodium nitroprusside is indicated for the immediate reduction of blood pressure of adult and pediatric patients in hypertensive crises. Concomitant longer-acting antihypertensive medication should be administered so that the duration of treatment with sodium nitroprusside injection can be minimized.

Sodium nitroprusside is also indicated for producing controlled hypotension in order to reduce bleeding during surgery.

Sodium nitroprusside is also indicated for the treatment of acute congestive heart failure.

CONTRAINDICATIONS

Sodium nitroprusside should not be used in the treatment of compensatory hypertension, where the primary hemodynamic lesion is aortic coarctation or arteriovenous shunting.

Sodium nitroprusside should not be used to produce hypotension during surgery in patients with known inadequate cerebral circulation, or in moribund patients (A.S.A. Class 5E) coming to emergency surgery.

Patients with congenital (Leber’s) optic atrophy or with tobacco amblyopia have unusually high cyanide/thiocyanate ratios. These rare conditions are probably associated with defective or absent rhodanase, and sodium nitroprusside should be avoided in these patients.

Sodium nitroprusside should not be used for the treatment of acute congestive heart failure associated with reduced peripheral vascular resistance such as high-output heart failure that may be seen in endotoxic sepsis.

WARNINGS

(See also the boxed warning at the beginning of this insert.)

The principal hazards of sodium nitroprusside administration are excessive hypotension and excessive accumulation of cyanide (see also OVERDOSAGE and DOSAGE AND ADMINISTRATION).

Excessive Hypotension: Small transient excesses in the infusion rate of sodium nitroprusside can result in excessive hypotension, sometimes to levels so low as to compromise the perfusion of vital organs. These hemodynamic changes may lead to a variety of associated symptoms; see ADVERSE REACTIONS. Nitroprusside-induced hypotension will be self-limited within 1 to 10 minutes after discontinuation of the nitroprusside infusion; during these few minutes, it may be helpful to put the patient into a head-down (Trendelenburg) position to maximize venous return. If hypotension persists more than a few minutes after discontinuation of the infusion of sodium nitroprusside, sodium nitroprusside is not the cause, and the true cause must be sought.

Cyanide Toxicity: As described in CLINICAL PHARMACOLOGYabove, sodium nitroprusside infusions at rates above 2 mcg/kg/min generate cyanide ion (CN^–) faster than the body can normally dispose of it. (When sodium thiosulfate is given, as described under DOSAGE AND ADMINISTRATION, the body’s capacity for CN^– elimination is greatly increased.) Methemoglobin normally present in the body can buffer a certain amount of CN^–, but the capacity of this system is exhausted by the CN^– produced from about 500 mcg/kg of sodium nitroprusside. This amount of sodium nitroprusside is administered in less than an hour when the drug is administered at 10 mcg/kg/min (the maximum recommended rate). Thereafter, the toxic effects of CN^– may be rapid, serious, and even lethal.

The true rates of clinically important cyanide toxicity cannot be assessed from spontaneous reports or published data. Most patients reported to have experienced such toxicity have received relatively prolonged infusions, and the only patients whose deaths have been unequivocally attributed to nitroprusside-induced cyanide toxicity have been patients who had received nitroprusside infusions at rates (30 to 120 mcg/kg/min) much greater than those now recommended. Elevated cyanide levels, metabolic acidosis, and marked clinical deterioration, however, have occasionally been reported in patients who received infusions at recommended rates for only a few hours and even, in one case, for only 35 minutes. In some of these cases, infusion of sodium thiosulfate caused dramatic clinical improvement, supporting the diagnosis of cyanide toxicity.

Cyanide toxicity may manifest itself as venous hyperoxemia with bright red venous blood, as cells become unable to extract the oxygen delivered to them; metabolic (lactic) acidosis; air hunger; confusion; and death. Cyanide toxicity due to causes other than nitroprusside has been associated with angina pectoris and myocardial infarction; ataxia, seizures, and stroke; and other diffuse ischemic damage.

Hypertensive patients, and patients concomitantly receiving other antihypertensive medications, may be more sensitive to the effects of sodium nitroprusside than normal subjects.

PRECAUTIONS

General

Like other vasodilators, sodium nitroprusside can cause increases in intracranial pressure. In patients whose intracranial pressure is already elevated, sodium nitroprusside should be used only with extreme caution.

Hepatic:

Use caution when administering nitroprusside to patients with hepatic insufficiency.

Use in Anesthesia:

When sodium nitroprusside (or any other vasodilator) is used for controlled hypotension during anesthesia, the patient’s capacity to compensate for anemia and hypovolemia may be diminished. If possible, pre-existing anemia and hypovolemia should be corrected prior to administration of sodium nitroprusside.

Hypotensive anesthetic techniques may also cause abnormalities of the pulmonary ventilation/perfusion ratio.

Patients intolerant of these abnormalities may require a higher fraction of inspired oxygen.Extreme caution should be exercised in patients who are especially poor surgical risks (A.S.A. Class 4 and 4E).

Laboratory Tests:

The cyanide-level assay is technically difficult, and cyanide levels in body fluids other than packed red blood cells are difficult to interpret. Cyanide toxicity will lead to lactic acidosis and venous hyperoxemia, but these findings may not be present until an hour or more after the cyanide capacity of the body’s red-cell mass has been exhausted

Drug Interactions

The hypotensive effect of sodium nitroprusside is augmented by that of most other hypotensive drugs, including ganglionic blocking agents, negative inotropic agents, and inhaled anesthetics.

Carcinogenesis, Mutagenesis, Impairment of Fertility

Animal studies assessing sodium nitroprusside’s carcinogenicity and mutagenicity have not been conducted. Similarly, sodium nitroprusside has not been tested for effects on fertility.

Pregnancy: Teratogenic Effects: Pregnancy: Category C.

There are no adequate, well-controlled studies of sodium nitroprusside in either laboratory animals or pregnant women.

It is not known whether sodium nitroprusside can cause fetal harm when administered to a pregnant woman or can affect reproductive capacity. Sodium nitroprusside should be given to a pregnant woman only if clearly needed

Nonteratogenic effects: In three studies in pregnant ewes, nitroprusside was shown to cross the placental barrier. Fetal cyanide levels were shown to be dose-related to maternal levels of nitroprusside. The metabolic transformation of sodium nitroprusside given to pregnant ewes led to fatal levels of cyanide in the fetuses. The infusion of 25 mcg/kg/min of sodium nitroprusside for one hour in pregnant ewes resulted in the death of all fetuses. Pregnant ewes infused with 1 mcg/kg/min of sodium nitroprusside for one hour delivered normal lambs.

According to one investigator, a pregnant woman at 24 weeks gestation was given sodium nitroprusside to control gestational hypertension secondary to mitral valve disease. Sodium nitroprusside was infused at 3.9 mcg/kg/min for a total of 3.5 mg/kg over 15 hours prior to delivery of a 478 gram stillborn infant without any obvious anomalies. Cyanide levels in the fetal liver were less than 10 mcg/mL. Toxic levels have been reported to be more than 30 to 40 mcg/mL. The mother demonstrated no cyanide toxicity.

The effects of administering sodium thiosulfate in pregnancy, either by itself or as a co-infusion with sodium nitroprusside, are completely unknown.

Nursing Mothers

It is not known whether sodium nitroprusside and its metabolites are excreted in human milk. Because many drugs are excreted in human milk and because of the potential for serious adverse reactions in nursing infants from sodium nitroprusside, a decision should be made whether to discontinue nursing or to discontinue the drug, taking into account the importance of the drug to the mother.

Pediatric Use

Efficacy in the pediatric population was established based on adult trials and supported by the dose-ranging trial (Study 1) and an open label trial of at least 12 hour infusion at a rate that achieved adequate MAP control (Study 2) with pediatric patients on sodium nitroprusside. No novel safety issues were seen in these studies in pediatric patients. See CLINICAL PHARMACOLOGY and DOSAGE AND ADMINISTRATION.

ADVERSE REACTIONS

The most important adverse reactions to sodium nitroprusside are the avoidable ones of excessive hypotension and cyanide toxicity, described above under WARNINGS. The adverse reactions described in this section develop less rapidly and, as it happens, less commonly.

Methemoglobinemia: As described in CLINICAL PHARMACOLOGYabove, sodium nitroprusside infusions can cause sequestration of hemoglobin as methemoglobin. The back-conversion process is normally rapid, and clinically significant methemoglobinemia (>10%) is seen only rarely in patients receiving sodium nitroprusside. Even patients congenitally incapable of back-converting methemoglobin should demonstrate 10% methemoglobinemia only after they have received about 10 mg/kg of sodium nitroprusside, and a patient receiving sodium nitroprusside at the maximum recommended rate (10 mcg/kg/min) would take over 16 hours to reach this total accumulated dose.

Methemoglobin levels can be measured by most clinical laboratories. The diagnosis should be suspected in patients who have received >10 mg/kg of sodium nitroprusside and who exhibit signs of impaired oxygen delivery despite adequate cardiac output and adequate arterial pO2. Classically, methemoglobinemic blood is described as chocolate brown, without color change on exposure to air. When methemoglobinemia is diagnosed, the treatment of choice is 1 to 2 mg/kg of methylene blue, administered intravenously over several minutes. In patients likely to have substantial amounts of cyanide bound to methemoglobin as cyanmethemoglobin, treatment of methemoglobinemia with methylene blue must be undertaken with extreme caution.

Thiocyanate Toxicity: As described in CLINICAL PHARMACOLOGYabove, most of the cyanide produced during metabolism of sodium nitroprusside is eliminated in the form of thiocyanate. When cyanide elimination is accelerated by the co-infusion of thiosulfate, thiocyanate production is increased.

Thiocyanate is mildly neurotoxic (tinnitus, miosis, hyperreflexia) at serum levels of 1 mmol/L (60 mg/L). Thiocyanate toxicity is life-threatening when levels are 3 or 4 times higher (200 mg/L). The steady-state thiocyanate level after prolonged infusions of sodium nitroprusside is increased with increased infusion rate, and the half-time of accumulation is 3 to 4 days. To keep the steady-state thiocyanate level below 1 mmol/L, a prolonged infusion of sodium nitroprusside should not be more rapid than 3 mcg/kg/min; in anuric patients, the corresponding limit is just 1 mcg/kg/min. When prolonged infusions are more rapid than these, thiocyanate levels should be measured daily.

Physiologic maneuvers (e.g., those that alter the pH of the urine) are not known to increase the elimination of thiocyanate. Thiocyanate clearance rates during dialysis, on the other hand, can approach the blood flow rate of the dialyzer.

Thiocyanate interferes with iodine uptake by the thyroid. Abdominal pain, apprehension, diaphoresis, “dizziness,” headache, muscle twitching, nausea, palpitations, restlessness, retching, and retrosternal discomfort have been noted when the blood pressure was too rapidly reduced. These symptoms quickly disappeared when the infusion was slowed or discontinued, and they did not reappear with a continued (or resumed) slower infusion.

Other adverse reactions reported are:

Cardiovascular: Bradycardia, electrocardiographic changes, tachycardia.

Dermatologic: Rash.

Endocrine: Hypothyroidism.

Gastrointestinal: Ileus.

Hematologic: Decreased platelet aggregation.

Neurologic: Increased intracranial pressure.

Miscellaneous: Flushing, venous streaking, irritation at the infusion site.

OVERDOSAGE

Overdosage of nitroprusside can be manifested as excessive hypotension or cyanide toxicity (see WARNINGS) or as thiocyanate toxicity (see ADVERSE REACTIONS). The acute intravenous mean lethal doses (LD50) of nitroprusside in rabbits, dogs, mice, and rats are 2.8, 5.0, 8.4, and 11.2 mg/kg, respectively.

Treatment of cyanide toxicity: Cyanide levels can be measured by many laboratories, and blood-gas studies that can detect venous hyperoxemia or acidosis are widely available. Acidosis may not appear until more than an hour after the appearance of dangerous cyanide levels, and laboratory tests should not be awaited. Reasonable suspicion of cyanide toxicity is adequate grounds for initiation of treatment.

Treatment of cyanide toxicity consists of

• discontinuing the administration of sodium nitroprusside;

• providing a buffer for cyanide by using sodium nitrite to convert as much hemoglobin into methemoglobin as the patient can safely tolerate; and then

• infusing sodium thiosulfate in sufficient quantity to convert the cyanide into thiocyanate.

The necessary medications for this treatment are contained in commercially available Cyanide Antidote Kits. Alternatively, discrete stocks of medications can be used. Hemodialysis is ineffective in removal of cyanide, but it will eliminate most thiocyanate. Cyanide Antidote Kits contain both amyl nitrite and sodium nitrite for induction of methemoglobinemia. The amyl nitrite is supplied in the form of inhalant ampoules, for administration in environments where intravenous administration of sodium nitrite may be delayed. In a patient who already has a patent intravenous line, use of amyl nitrite confers no benefit that is not provided by infusion of sodium nitrite.

Sodium nitrite is available in a 3% solution, and 4 to 6 mg/kg (about 0.2 mL/kg) should be injected over 2 to 4 minutes. This dose can be expected to convert about 10% of the patient’s hemoglobin into methemoglobin; this level of methemoglobinemia is not associated with any important hazard of its own. The nitrite infusion may cause transient vasodilatation and hypotension, and this hypotension must, if it occurs, be routinely managed.

Immediately after infusion of the sodium nitrite, sodium thiosulfate should be infused. This agent is available in 10% and 25% solutions, and the recommended dose is 150 to 200 mg/kg; a typical adult dose is 50 mL of the 25% solution. Thiosulfate treatment of an acutely cyanide-toxic patient will raise thiocyanate levels, but not to a dangerous degree. The nitrite/thiosulfate regimen may be repeated, at half the original doses, after two hours.

DOSAGE AND ADMINISTRATION

Dilution to proper strength for infusion: Depending on the desired concentration, the solution containing 50 mg of sodium nitroprusside must be further diluted in 250 to 1000 mL of sterile 5% dextrose injection. The diluted solution should be protected from light, using the supplied opaque sleeve, aluminum foil, or other opaque material. It is not necessary to cover the infusion drip chamber or the tubing.

Verification of the chemical integrity of the product: Sodium nitroprusside solution can be inactivated by reactions with trace contaminants. The products of these reactions are often blue, green, or red, much brighter than the faint brownish color of unreacted sodium nitroprusside injection. Discolored solutions, or solutions in which particulate matter is visible, should not be used. If properly protected from light, the freshly diluted solution is stable for 24 hours.

No other drugs should be administered in the same solution with sodium nitroprusside. Avoidance of excessive hypotension: While the average effective rate in adult and pediatric patients is about 3 mcg/kg/min, some patients will become dangerously hypotensive when they receive sodium nitroprusside at this rate.

Infusion of sodium nitroprusside should therefore be started at a very low rate (0.3 mcg/kg/min), with upward titration every few minutes until the desired effect is achieved or the maximum recommended infusion rate (10 mcg/kg/min) has been reached.

Because sodium nitroprusside’s hypotensive effect is very rapid in onset and in dissipation, small variations in infusion rate can lead to wide, undesirable variations in blood pressure. Since there is inherent variation in blood pressure measurement, confirm the drug effect at any infusion rate after an additional 5 minutes before titrating to a higher dose to achieve the desired blood pressure. Sodium nitroprusside should not be infused through ordinary I.V. apparatus, regulated only by gravity and mechanical clamps. Only an infusion pump, preferably a volumetric pump, should be used.

Because sodium nitroprusside can induce essentially unlimited blood-pressure reduction, the blood pressure of a patient receiving this drug must be continuously monitored, using either a continually reinflated sphygmomanometer or (preferably) an intra-arterial pressure sensor. Special caution should be used in elderly patients, since they may be more sensitive to the hypotensive effects of the drug.

When sodium nitroprusside is used in the treatment of acute congestive heart failure, titration of the infusion rate must be guided by the results of invasive hemodynamic monitoring with simultaneous monitoring of urine output. Sodium nitroprusside can be titrated by increasing the infusion rate until:

• measured cardiac output is no longer increasing,

• systemic blood pressure cannot be further reduced without compromising the perfusion of vital organs, or

• the maximum recommended infusion rate has been reached, whichever comes earliest. Specific hemodynamic goals must be tailored to the clinical situation, but improvements in cardiac output and left ventricular filling pressure must not be purchased at the price of undue hypotension and consequent hypoperfusion.

Table 2 below shows the infusion rates corresponding to the recommended initial and maximal doses (0.3 mcg/kg/min and 10 mcg/kg/min, respectively) for both adult and pediatric patients of various weights. This infusion rate may be lower than indicated in the table for patients less than 10 kg. Note that when the concentration used in a given patient is changed, the tubing is still filled with a solution at the previous concentration.

Table 2: Infusion Rates (mL/hour) to Achieve Initial (0.3 mcg/kg/min) and Maximal (10 mcg/kg/min) Dosing of Sodium Nitroprusside

Volume Sodium | Nitroprusside concentration |  | 250 mL 50 mg 200 mcg/mL |  | 500 mL 50 mg 100 mcg /mL |  | 1000 mL 50 mg 50 mcg /mL
pt kg | weight lbs |  | init | max | init | max | init | max
10 | 22 |  | 1 | 30 | 2 | 60 | 4 | 120
20 | 44 |  | 2 | 60 | 4 | 120 | 7 | 240
30 | 66 |  | 3 | 90 | 5 | 180 | 11 | 360
40 | 88 |  | 4 | 120 | 7 | 240 | 14 | 480
50 | 110 |  | 5 | 150 | 9 | 300 | 18 | 600
60 | 132 |  | 5 | 180 | 11 | 360 | 22 | 720
70 | 154 |  | 6 | 210 | 13 | 420 | 25 | 840
80 | 176 |  | 7 | 240 | 14 | 480 | 29 | 960
90 | 198 |  | 8 | 270 | 16 | 540 | 32 | 1080
100 | 220 |  | 9 | 300 | 18 | 600 | 36 | 1200

Avoidance of cyanide toxicity: As described in CLINICAL PHARMACOLOGYabove, when more than 500 mcg/kg of sodium nitroprusside is administered faster than 2 mcg/kg/min, cyanide is generated faster than the unaided patient can eliminate it. Administration of sodium thiosulfate has been shown to increase the rate of cyanide processing, reducing the hazard of cyanide toxicity. Although toxic reactions to sodium thiosulfate have not been reported, the co-infusion regimen has not been extensively studied, and it cannot be recommended without reservation. In one study, sodium thiosulfate appeared to potentiate the hypotensive effects of sodium nitroprusside.

Co-infusions of sodium thiosulfate have been administered at rates of 5 to 10 times that of sodium nitroprusside.

Care must be taken to avoid the indiscriminate use of prolonged or high doses of sodium nitroprusside with sodium thiosulfate as this may result in thiocyanate toxicity and hypovolemia. Incautious administration of sodium nitroprusside must still be avoided, and all of the precautions concerning sodium nitroprusside administration must still be observed.

Consideration of methemoglobinemia and thiocyanate toxicity: Rare patients receiving more than 10 mg/kg of sodium nitroprusside will develop methemoglobinemia; other patients, especially those with impaired renal function, will predictably develop thiocyanate toxicity after prolonged, rapid infusions. In accordance with the descriptions in ADVERSE REACTIONS above, patients with suggestive findings should be tested for these toxicities.

WARNING: Do not use flexible container in series connections

HOW SUPPLIED

Sodium nitroprusside injection is supplied in amber-colored, single-dose 50 mg/2 mL Vials (NDC 75907-290-11).

Store at 20° to 25°C (68° to 77°F). [See USP Controlled Room Temperature.]

To protect sodium nitroprusside injection from light, it should be stored in its carton until it is used.

To report SUSPECTED ADVERSE REACTIONS, contact Dr. REDDY'S LABORATORIES Inc., at 1-888-375-3784 or FDA at 1-800-FDA-1088or www.fda.gov/medwatch.

Rx Only

Distributor:

Dr. Reddy’s Laboratories Inc.,

Princeton, NJ 08540

Made in INDIA

PREMIERProRx® is a registered trademark of Premier Healthcare Alliance, L.P., used under license

Issued: 03/2025